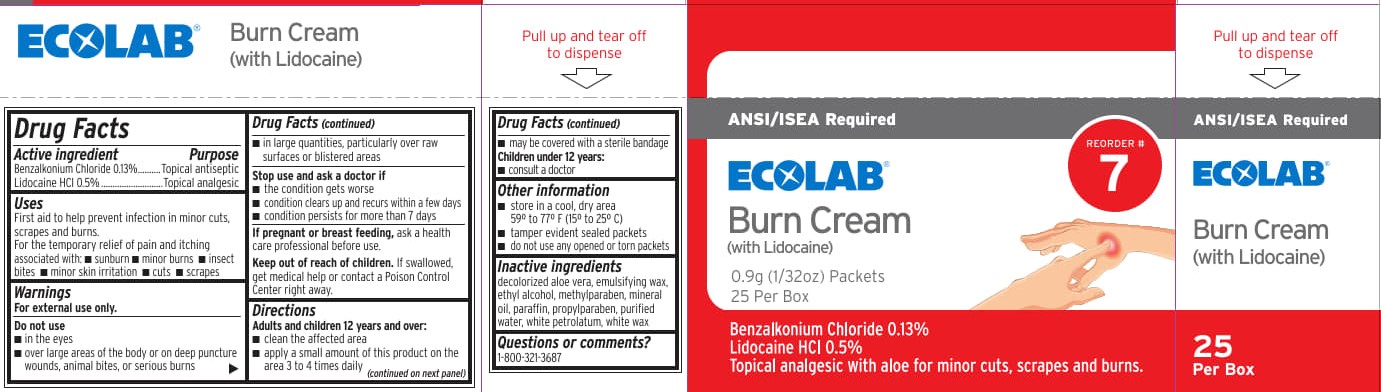 DRUG LABEL: ECOLAB Burn Cream
NDC: 71338-123 | Form: CREAM
Manufacturer: ECOLAB Food Safety Specialties, Inc.
Category: otc | Type: HUMAN OTC DRUG LABEL
Date: 20250909

ACTIVE INGREDIENTS: LIDOCAINE HYDROCHLORIDE 5 mg/1 g; BENZALKONIUM CHLORIDE 1.3 mg/1 g
INACTIVE INGREDIENTS: ALOE VERA LEAF; WATER; PETROLATUM; WHITE WAX; PROPYLPARABEN; PARAFFIN; ALCOHOL; METHYLPARABEN; MINERAL OIL

ECOLAB Burn Cream

Drug Facts

Active ingredient

Benzalkonium Chloride 0.13%

Lidocaine HCl 0.5%

Purpose

Topical antiseptic

Topical analgesic

Uses

First aid to help prevent infection in minor cuts, scrapes and burns.

For the temporary relif of pain and itching associated with:

- sunburn
- minor burns
- insect bites
- minor skin irritation
- cuts
- scrapes

Warnings

For external use only.

Do not use

- in the eyes
- over large areas of the body or on deep puncture wounds, animal bites or serious burns
- in large quantities, particularly over raw surfaces or blistered areas

Stop use and ask a doctor if

- condition gets worse
- condition clears up and recurs within a few days
- condition persists for more than 7 days

PREGNANCY OR BREAST FEEDING

If pregnant or breast feeding, ask a health care professional before use.

Keep out of reach of children.

If swallowed, get medical help or call a Poison Control Center right away.

Directions

Adults and children 12 years and over

- clean the affected area
- apply a small amount of this product on the area 3 times daily
- may be covered with a sterile bandage

Children under 12 years

- consult a doctor

Other information

- store in a cool dry area 59° to 79°F (15° to 25°C)
- tamper evident sealed packets
- do not use any opened or torn packets

Inactive ingredients

decolorized aloe vera, emulsifying wax, ethyl alcohol, methylparaben, mineral oil, paraffin, propylparaben, purified water, white petrolatum, white wax

Questions or comments? 1-800-321-3687

ECOLAB Burn Cream Label

ANSI/ISEA Required

ECOLAB®

Burn Cream

(with Lidocaine)

Reorder # 7

0.9g (1/32oz) Packets

25 per Box

Benzalkonium Chloride 0.13%

Lidocaine HCl 0.5%

Topical analgesic with aloe

for minor cuts, scrapes and burns